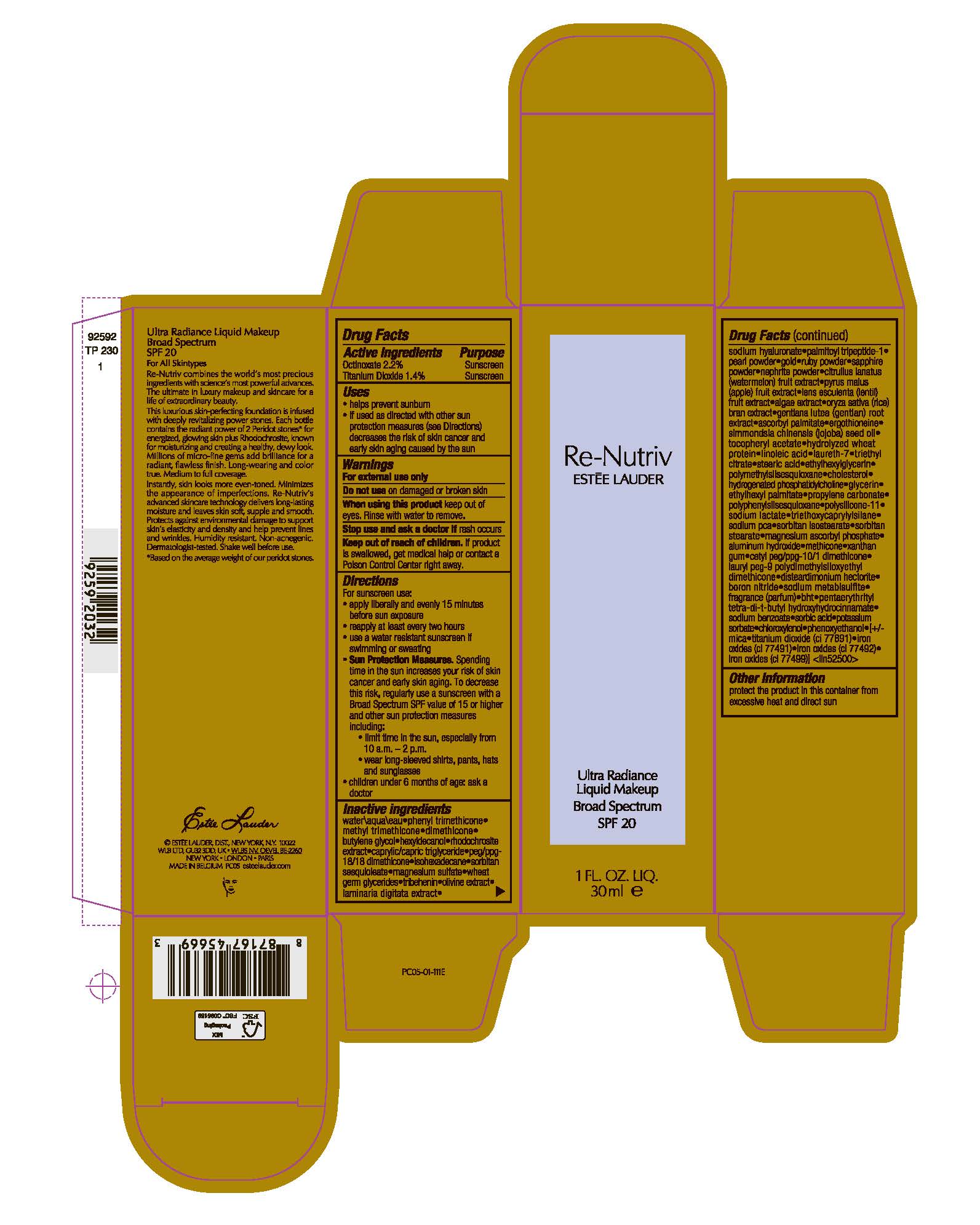 DRUG LABEL: RE-NUTRIV ULTRA RADIANCE MAKEUP BROAD SPECTRUM SPF 20
NDC: 11559-057 | Form: LIQUID
Manufacturer: ESTEE LAUDER INC
Category: otc | Type: HUMAN OTC DRUG LABEL
Date: 20251229

ACTIVE INGREDIENTS: OCTINOXATE 22 mg/1 mL; TITANIUM DIOXIDE 14 mg/1 mL
INACTIVE INGREDIENTS: WATER; PHENYL TRIMETHICONE; METHYL TRIMETHICONE; DIMETHICONE; BUTYLENE GLYCOL; ISOCETYL ALCOHOL; PEG/PPG-18/18 DIMETHICONE; MEDIUM-CHAIN TRIGLYCERIDES; ISOHEXADECANE; SORBITAN SESQUIOLEATE; MAGNESIUM SULFATE, UNSPECIFIED FORM; WHEAT GERM OIL; TRIBEHENIN; LAMINARIA DIGITATA; HYALURONATE SODIUM; PALMITOYL TRIPEPTIDE-1; PEARL (HYRIOPSIS CUMINGII); GOLD; WATERMELON; APPLE; LENS CULINARIS FRUIT; RICE BRAN; GENTIANA LUTEA ROOT; ASCORBYL PALMITATE; ERGOTHIONEINE; JOJOBA OIL; .ALPHA.-TOCOPHEROL ACETATE; HYDROLYZED WHEAT PROTEIN (ENZYMATIC; 3000 MW); LINOLEIC ACID; LAURETH-7; TRIETHYL CITRATE; STEARIC ACID; ETHYLHEXYLGLYCERIN; POLYMETHYLSILSESQUIOXANE (4.5 MICRONS); CHOLESTEROL; HYDROGENATED SOYBEAN LECITHIN; GLYCERIN; ETHYLHEXYL PALMITATE; PROPYLENE CARBONATE; DIMETHICONE/VINYL DIMETHICONE CROSSPOLYMER (SOFT PARTICLE); SODIUM LACTATE; TRIETHOXYCAPRYLYLSILANE; TOCOPHEROL; SODIUM PYRROLIDONE CARBOXYLATE; SORBITAN ISOSTEARATE; SORBITAN MONOSTEARATE; MAGNESIUM ASCORBYL PHOSPHATE; ALUMINUM HYDROXIDE; METHICONE (20 CST); XANTHAN GUM; LAURYL PEG-9 POLYDIMETHYLSILOXYETHYL DIMETHICONE; DISTEARDIMONIUM HECTORITE; BORON NITRIDE; SODIUM METABISULFITE; BUTYLATED HYDROXYTOLUENE; PENTAERYTHRITOL TETRAKIS(3-(3,5-DI-TERT-BUTYL-4-HYDROXYPHENYL)PROPIONATE); SORBIC ACID; SODIUM BENZOATE; POTASSIUM SORBATE; CHLOROXYLENOL; PHENOXYETHANOL; MICA; FERRIC OXIDE YELLOW; FERRIC OXIDE RED; FERROSOFERRIC OXIDE

RE-NUTRIV ULTRA RADIANCE LIQUID MAKEUP BROAD SPECTRUM SPF 20

Drug Facts

ACTIVE INGREDIENT

Active ingredients | Purpose
Octinoxate 2.2% | Sunscreen
Titanium Dioxide 1.4% | Sunscreen

Use

helps prevent sunburn

Warnings

For external use only

Do not use on damaged or broken skin

When using this product keep out of eyes. Rinse with water to remove.

Stop use and ask a doctor if rash occurs

Keep out of reach of children. If product is swallowed, get medical help or contact a Poison Control Center right away.

Directions

For sunscreen use:

- apply liberally 15 minutes before sun exposure
- reapply at least every two hours
- use a water resistant sunscreen if swimming or sweating
- Sun Protection Measures. Spending time in the sun increases your risk of skin cancer and early skin aging. To decrease this risk, regularly use a sunscreen with a Broad Spectrum SPF value of 15 or higher and other sun protection measures including:
  - limit time in the sun, especially from 10 a.m. – 2 p.m.
  - wear long-sleeved shirts, pants, hats and sunglasses
- children under 6 months of age: ask a doctor

Inactive ingredients

water\aqua\eau • phenyl trimethicone • methyl trimethicone • dimethicone • butylene glycol • isocetyl alcohol • peg/ppg-18/18 dimethicone • rhodochrosite extract • caprylic/capric triglyceride • isohexadecane • sorbitan sesquioleate • magnesium sulfate • wheat germ glycerides • tribehenin • olivine extract • laminaria digitata extract • sodium hyaluronate • trifluoroacetyl tripeptide-2 • palmitoyl tripeptide-1 • pearl powder • gold • ruby powder • sapphire powder • nephrite powder • citrullus vulgaris (watermelon) fruit extract • pyrus malus (apple) fruit extract • lens esculenta (lentil) fruit extract • algae extract • oryza sativa (rice) bran extract • gentiana lutea (gentian) root extract • ascorbyl palmitate • ergothioneine • simmondsia chinensis (jojoba) seed oil • tocopheryl acetate • hydrolyzed wheat protein • linoleic acid • laureth-7 • triethyl citrate • stearic acid • ethylhexylglycerin • polymethylsilsesquioxane • cholesterol • hydrogenated lecithin • glycerin • ethylhexyl palmitate • propylene carbonate • polyphenylsilsesquioxane • polysilicone-11 • sodium lactate • triethoxycaprylylsilane • tocopherol • sodium pca • sorbitan isostearate • sorbitan stearate • magnesium ascorbyl phosphate • aluminum hydroxide • methicone • xanthan gum • cetyl peg/ppg-10/1 dimethicone • lauryl peg-9 polydimethylsiloxyethyl dimethicone • disteardimonium hectorite • dextran • boron nitride • sodium metabisulfite • fragrance (parfum) • bht • pentaerythrityl tetra-di-t-butyl hydroxyhydrocinnamate • sorbic acid • sodium benzoate • potassium sorbate • chloroxylenol • phenoxyethanol • [+/- mica • titanium dioxide (ci 77891) • iron oxides (ci 77492) • iron oxides (ci 77491) • iron oxides (ci 77499)] <iln46282>

Other information

protect the product in this container from excessive heat and direct sun

PRINCIPAL DISPLAY PANEL - 30 ml Tube Carton

Re-Nutriv
ESTĒE LAUDER

Ultra Radiance
Liquid Makeup

Broad Spectrum

SPF 20

1 FL. OZ. LIQ.
30 ml e